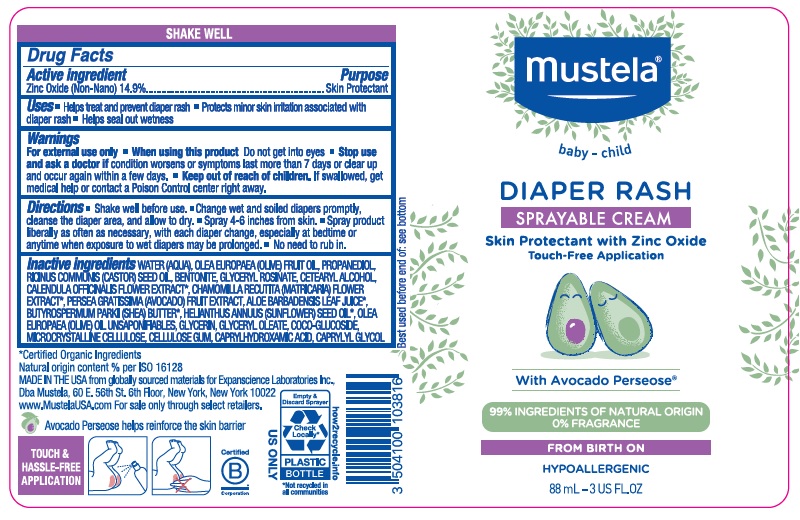 DRUG LABEL: Mustela Diaper Rash Sprayable
NDC: 64768-2928 | Form: CREAM
Manufacturer: Expanscience Laboratories d/b/a Mustela
Category: otc | Type: HUMAN OTC DRUG LABEL
Date: 20241202

ACTIVE INGREDIENTS: ZINC OXIDE 149 mg/1 mL
INACTIVE INGREDIENTS: BENTONITE; CHAMOMILE; COCO GLUCOSIDE; CETOSTEARYL ALCOHOL; OLIVE OIL; PROPANEDIOL; CASTOR OIL; GLYCERYL ROSINATE; CAPRYLHYDROXAMIC ACID; CAPRYLYL GLYCOL; GLYCERYL OLEATE; GLYCERIN; SUNFLOWER OIL; CALENDULA OFFICINALIS FLOWER; AVOCADO; ALOE VERA LEAF; OLEA EUROPAEA (OLIVE) OIL UNSAPONIFIABLES; MICROCRYSTALLINE CELLULOSE; CARBOXYMETHYLCELLULOSE SODIUM, UNSPECIFIED FORM; SHEA BUTTER; WATER

Mustela Diaper Rash Sprayable Cream

Active ingredient

Zinc Oxide (Non-Nano) 14.9%

Purpose

Skin Protectant

Uses

- Helps treat and prevent diaper rash
- Protects minor skin irritation associated with diaper rash
- Helps seal out wetness

Warnings

For external use only.

When using this product

do not get into eyes

Stop use and ask a doctor if

condition worsens or symptoms last more than 7 days or clear up and occur again within a few days.

Keep out of reach of children.

If swallowed, get medical help or contact a Poison Control Center right away.

Directions

- Shake well before use.
- Change wet and soiled diapers promptly, cleanse the diaper area, and allow to dry.
- Spray 4-6 inches from skin.
- Spray product liberally as often as necessary, with each diaper change, especially at bedtime or anytime when exposure to wet diapers may be prolonged.
- No need to rub in.

Inactive ingredients

WATER (AQUA), OLEA EUROPAEA (OLIVE) FRUIT OIL, PROPANEDIOL, RICINUS COMMUNIS (CASTOR) SEED OIL, BENTONITE, GLYCERYL ROSINATE, CETEARYL ALCOHOL, CALENDULA OFFICINALIS FLOWER EXTRACT*, CHAMOMILLA RECUTITA (MATRICARIA) FLOWER EXTRACT*, PERSEA GRATISSIMA (AVOCADO) FRUIT EXTRACT, ALOE BARBADENSIS LEAF JUICE*, BUTYROSPERMUM PARKII (SHEA) BUTTER*, HELIANTHUS ANNUUS (SUNFLOWER) SEED OIL*, OLEA EUROPAEA (OLIVE) OIL UNSAPONIFIABLES, GLYCERIN, GLYCERYL OLEATE, COCO-GLUCOSIDE, MICROCRYSTALLINE CELLULOSE, CELLULOSE GUM, CAPRYLHYDROXAMIC ACID, CAPRYLYL GLYCOL

*Certified Organic Ingredients

Company information

MADE IN THE USA from globally sourced materials for Expanscience Laboratories Inc., Dba Mustela, 60 E. 56th St. 6th Floor, New York, New York 10022 www.MustelaUSA.com For sale only through select retailers.